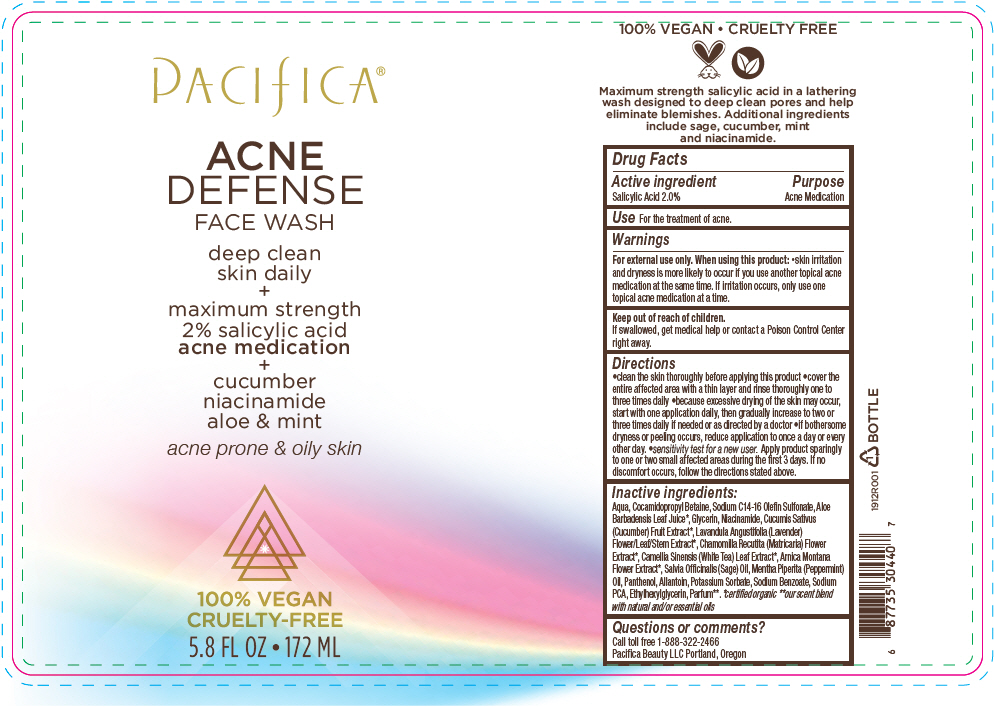 DRUG LABEL: ACNE DEFENSE FACE WASH
NDC: 61197-100 | Form: LIQUID
Manufacturer: Pacifica Beauty LLC.
Category: otc | Type: HUMAN OTC DRUG LABEL
Date: 20200106

ACTIVE INGREDIENTS: Salicylic Acid 20 mg/1 mL
INACTIVE INGREDIENTS: Water; Cocamidopropyl Betaine; Sodium C14-16 Olefin Sulfonate; Aloe Vera Leaf; Glycerin; Niacinamide; Cucumber; Lavandula angustifolia subsp. Angustifolia flowering top; Chamomile; White Tea; Arnica Montana Flower; Sage Oil; Peppermint Oil; Panthenol; Allantoin; Potassium Sorbate; Sodium Benzoate; Sodium Pyrrolidone Carboxylate; Ethylhexylglycerin

ACNE DEFENSE FACE WASH

Drug Facts

Active ingredient

Salicylic Acid 2.0%

Purpose

Acne Medication

Use

For the treatment of acne.

Warnings

For external use only.

When using this product

- skin irritation and dryness is more likely to occur if you use another topical acne medication at the same time. If irritation occurs, only use one topical acne medication at a time.

Keep out of reach of children.

If swallowed, get medical help or contact a Poison Control Center right away.

Directions

- clean the skin thoroughly before applying this product
- cover the entire affected area with a thin layer and rinse thoroughly one to three times daily
- because excessive drying of the skin may occur, start with one application daily, then gradually increase to two or three times daily if needed or as directed by a doctor
- if bothersome dryness or peeling occurs, reduce application to once a day or every other day.
- sensitivity test for a new user. Apply product sparingly to one or two small affected areas during the first 3 days. If no discomfort occurs, follow the directions stated above.

Inactive ingredients

Aqua, Cocamidopropyl Betaine, Sodium C14-16 Olefin Sulfonate, Aloe Barbadensis Leaf Juice [certified organic] , Glycerin, Niacinamide, Cucumis Sativus (Cucumber) Fruit Extract, Lavandula Angustifolia (Lavender) Flower/Leaf/Stem Extract, Chamomilla Recutita (Matricaria) Flower Extract, Camellia Sinensis (White Tea) Leaf Extract, Arnica Montana Flower Extract, Salvia Officinalis (Sage) Oil, Mentha Piperita (Peppermint) Oil, Panthenol, Allantoin, Potassium Sorbate, Sodium Benzoate, Sodium PCA, Ethylhexylglycerin, Parfum [our scent blend with natural and/or essential oils] .

Questions or comments?

Call toll free 1-888-322-2466

Pacifica Beauty LLC Portland, Oregon

PRINCIPAL DISPLAY PANEL - 172 ML Bottle Label

PACIFICA®

ACNE
DEFENSE
FACE WASH

deep clean
skin daily
+
maximum strength
2% salicylic acid
acne medication
+
cucumber
niacinamide
aloe & mint
acne prone & oily skin

100% VEGAN
CRUELTY-FREE

5.8 FL OZ • 172 ML